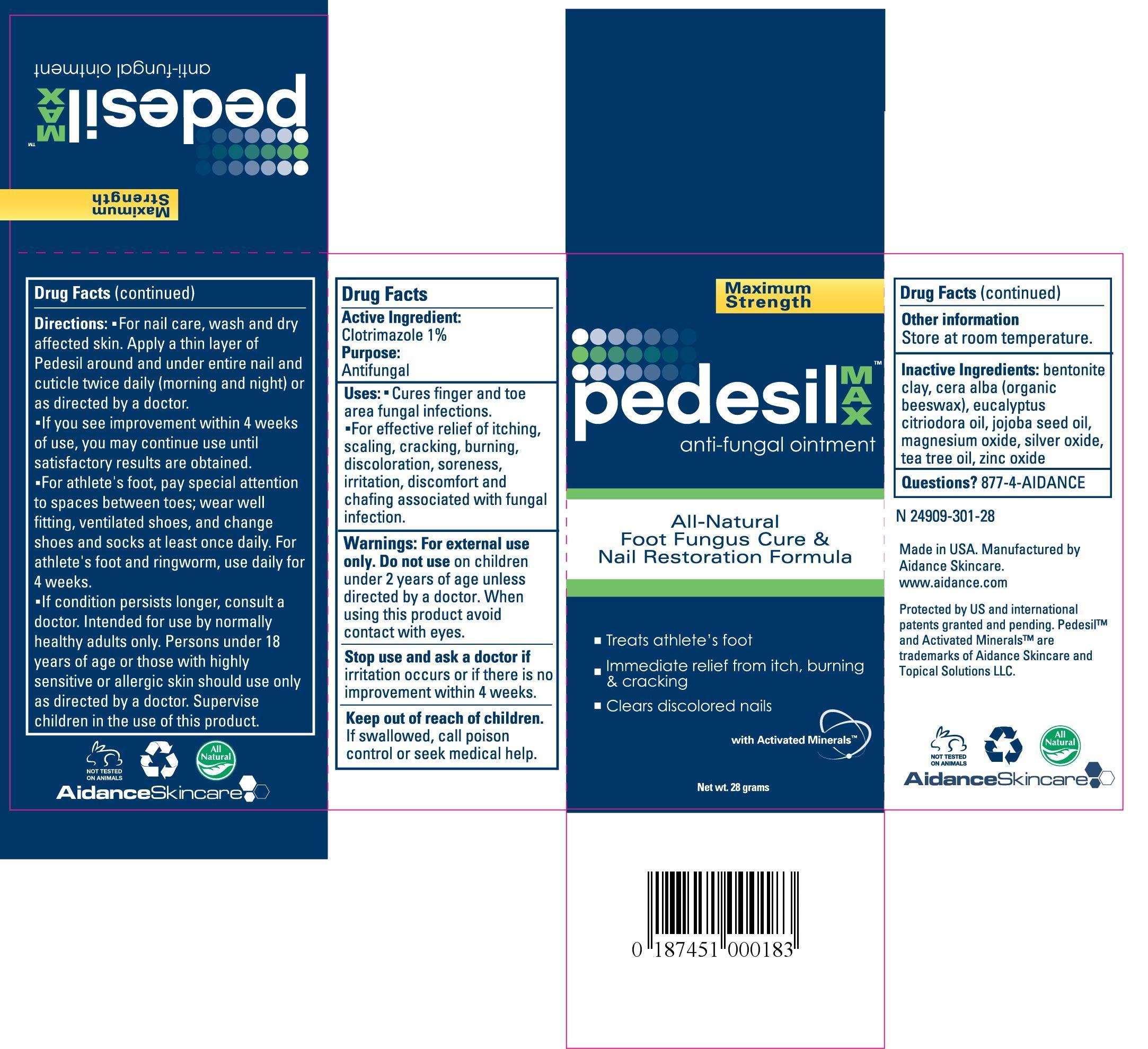 DRUG LABEL: Pedesil
NDC: 24909-301 | Form: OINTMENT
Manufacturer: Aidance Skincare & Topical Solutions, LLC
Category: otc | Type: HUMAN OTC DRUG LABEL
Date: 20120907

ACTIVE INGREDIENTS: CLOTRIMAZOLE 1.0 g/100 g
INACTIVE INGREDIENTS: BENTONITE; EUCALYPTUS OIL; JOJOBA OIL; MAGNESIUM OXIDE; SILVER OXIDE; TEA TREE OIL; WHITE WAX; ZINC OXIDE

Drug Facts

Active Ingredient

Clotrimazole 1%

Purpose

Antifungal

Uses

- Cures finger and toe area fungal infections.

- For effective relief of itching, scaling, cracking, burning, discoloration, soreness, irritation, discomfort and chafing associated with fungal infection.

Warnings

For external use only. Do not use on children under 2 years of age unless directed by a doctor. When using this product avoid contact with eyes.

Keep out of reach of children.

If swallowed, call poison control or seek medical help.

STOP USE

Stop and use and ask a doctor if irritation occurs or there is no improvement within 4 weeks.

Directions

- For nail care, wash and dry affected skin. Apply a thin layer of Pedesil around and under entire nail and cuticle twice daily (morning and night) or as directed by a doctor.

- If you see improvement within 4 weeks of use, you may continue use until satisfactory results are obtained.

- For athlete's foot, pay special attention to spaces between toes; wear well fitting, ventilated shoes, and change shoes and socks at least once daily. For athlete's foot and ringworm, use daily for 4 weeks.

- If condition persists longer, consult a doctor. Intended for use by normally healthy adults only. Persons under 18 years of age or those with highly sensitive or allergic skin should use only as directed by a doctor. Supervise children in the use of this product.

Other Information

Store at room temperature.

Other Ingredients

Beeswax, Bentonite, Eucalyptus Citriodora Oil, Jojoba Seed Oil, Magnesium Oxide, Silver Oxide, Tea Tree Oil,
Zinc Oxide.

Questions? 877-4-AIDANCE